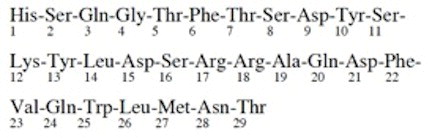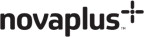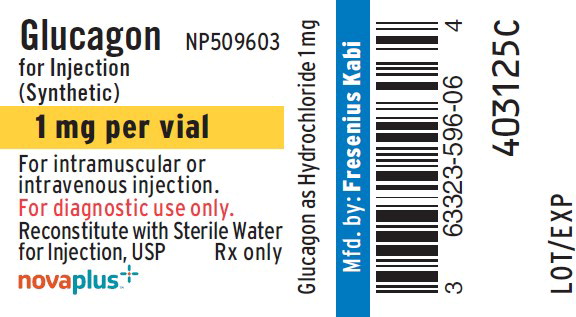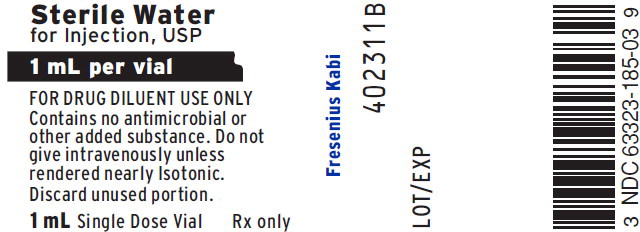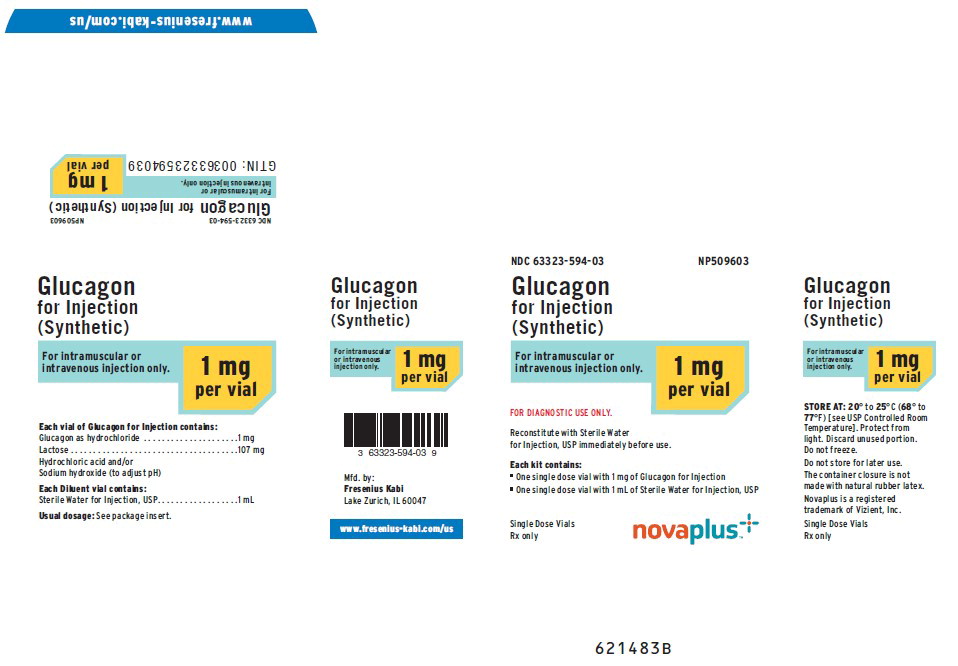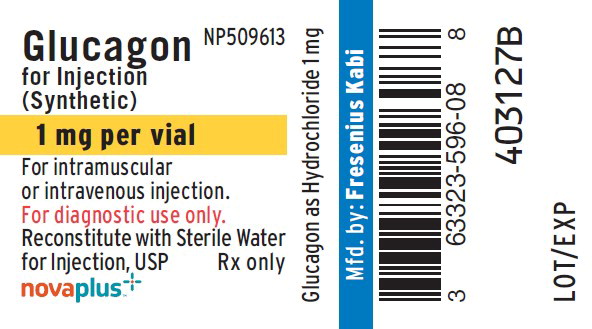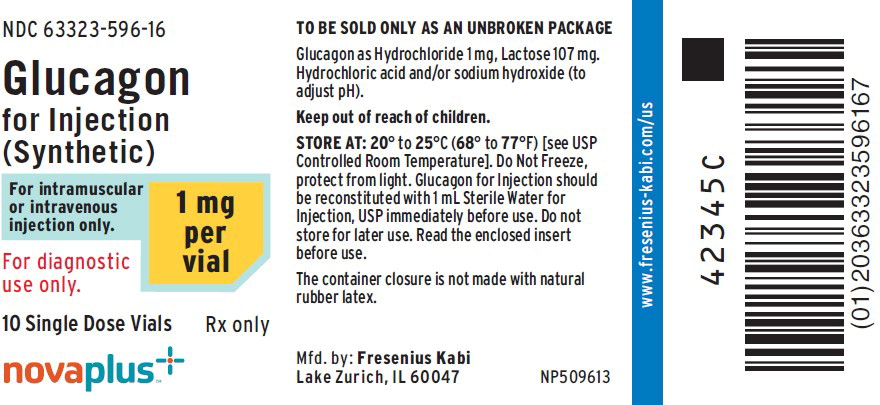 DRUG LABEL: Glucagon
NDC: 63323-596 | Form: INJECTION, POWDER, LYOPHILIZED, FOR SOLUTION
Manufacturer: Fresenius Kabi USA, LLC
Category: prescription | Type: HUMAN PRESCRIPTION DRUG LABEL
Date: 20220401

ACTIVE INGREDIENTS: GLUCAGON HYDROCHLORIDE 1 mg/1 mL
INACTIVE INGREDIENTS: LACTOSE MONOHYDRATE; HYDROCHLORIC ACID; SODIUM HYDROXIDE

HIGHLIGHTS OF PRESCRIBING INFORMATION

These highlights do not include all the information needed to use GLUCAGON FOR INJECTION safely and effectively. See full prescribing information for GLUCAGON FOR INJECTION.
GLUCAGON for injection, for intravenous or intramuscular use
Initial U.S. Approval: 1998

1 INDICATIONS AND USAGE

Glucagon for Injection is a gastrointestinal motility inhibitor indicated for use as a diagnostic aid during radiologic examinations to temporarily inhibit movement of the gastrointestinal (GI) tract (1)

Limitations of Use:

Glucagon for Injection is not indicated for the emergency treatment of hypoglycemia (1)

2 DOSAGE AND ADMINISTRATION

- Reconstitute lyophilized powder with Sterile Water for Injection before use (2.2, 2.3)
- Determine dose based on diagnostic procedure, route of administration and procedure duration (2.1):
  - To inhibit stomach and small bowel motility the dose is 0.2 mg to 0.5 mg given intravenously or 1 mg given intramuscularly
  - To inhibit colon motility the dose is 0.5 mg to 0.75 mg given intravenously or 1 mg to 2 mg given intramuscularly

3 DOSAGE FORMS AND STRENGTHS

For Injection: 1 mg lyophilized powder in single dose vial for reconstitution (3)

4 CONTRAINDICATIONS

- Pheochromocytoma (4, 5.1)
- Insulinoma (4, 5.2)
- Glucagonoma (4, 5.2)

5 WARNINGS AND PRECAUTIONS

- Hyperglycemia in patients with diabetes: Monitor blood glucose and treat with insulin if indicated (5.3)
- Increased blood pressure and heart rate in patients with cardiac disease: Monitor patients with known cardiac disease (5.4)
- Allergic reactions including anaphylactic shock with breathing difficulties, and hypotension, generalized rash: Discontinue and treat as indicated (5.5)

6 ADVERSE REACTIONS

Adverse reactions seen with glucagon are transient changes in blood pressure, increase in heart rate, hypersensitivity reactions, nausea and vomiting, and hypoglycemia (6)

To report SUSPECTED ADVERSE REACTIONS, contact Fresenius Kabi USA, LLC at 1-800-551-7176 or FDA at 1-800-FDA-1088 or www.fda.gov/medwatch.

7 DRUG INTERACTIONS

- Beta-blockers: May cause a greater increase in both heart rate and blood pressure (7)
- Insulin: Reacts antagonistically towards glucagon; monitor glucose (7)
- Indomethacin: May produce hypoglycemia; monitor glucose (7)
- Anticholinergic Drugs: Concomitant use not recommended due to increased gastrointestinal adverse reactions (7)
- Warfarin: May increase anticoagulant effect of warfarin; may require an adjustment in warfarin dosage (7)

FULL PRESCRIBING INFORMATION

1 INDICATIONS AND USAGE

Glucagon for Injection is indicated for use as a diagnostic aid during radiologic examinations to temporarily inhibit movement of the gastrointestinal tract.

Limitations of Use:

Glucagon for Injection is not indicated for the emergency treatment of hypoglycemia because it is not packaged with a syringe and diluent necessary for rapid preparation and administration during an emergency outside of a healthcare facility.

2 DOSAGE AND ADMINISTRATION

2.1 Recommended Dose

Determine the dose based on the type of diagnostic procedure, the route of administration and expected procedure duration [see Clinical Pharmacology (12.2)].

The usual dose to inhibit movement of the:

- Stomach and small bowel is 0.2 mg to 0.5 mg given intravenously or 1 mg given intramuscularly.
- Colon is 0.5 mg to 0.75 mg given intravenously or 1 mg to 2 mg given intramuscularly.

Bolus doses above 1 mg administered intravenously have caused nausea and vomiting and are not recommended [see Adverse Reactions (6)].

2.2 Reconstitution of the Lyophilized Powder

Glucagon for Injection is a lyophilized powder, which requires reconstitution with Sterile Water for Injection prior to intravenous or intramuscular use.

- Using a syringe, withdraw 1 mL of Sterile Water for Injection and inject into the vial containing Glucagon for Injection lyophilized powder.
- Shake the vial gently until the powder is completely dissolved and no particles remain in the reconstituted solution.
- Visually inspect the reconstituted solution for particulate matter and discoloration prior to administration. The reconstituted solution should be clear and of water-like consistency. Discard the reconstituted solution if there are signs of gel formation or particles.
- The reconstituted solution has a concentration of approximately 1 mg of glucagon per mL.
- Use the reconstituted glucagon immediately after reconstitution.

2.3 Important Administration Instructions

- Glucagon for Injection must be administered by medical personnel.
- The timing of administration of Glucagon for Injection depends upon the organ under examination and route of administration [see Clinical Pharmacology (12.2)].
- If given intravenously, administer Glucagon for Injection as a bolus over a time period of 1 minute.
- Discard any unused portion.
- After the end of the diagnostic procedure, give oral carbohydrates to patients who have been fasting, if this is compatible with the diagnostic procedure.

3 DOSAGE FORMS AND STRENGTHS

For injection: 1 mg of lyophilized powder in single dose vial for reconstitution.

4 CONTRAINDICATIONS

Glucagon for Injection is contraindicated in patients with:

- Pheochromocytoma [see Warnings and Precautions (5.1)] because of the risk of increased blood pressure
- Insulinoma [see Warnings and Precautions (5.2)] because of the risk of hypoglycemia
- Glucagonoma [see Warnings and Precautions (5.2)] because of the risk of hypoglycemia

5 WARNINGS AND PRECAUTIONS

5.1 Hypertension in Patients with Pheochromocytoma

Glucagon for Injection is contraindicated in patients with pheochromocytoma because glucagon may stimulate the release of catecholamines from the tumor, which may result in a sudden and marked increase in blood pressure.

5.2 Hypoglycemia in Patients with Insulinoma or Glucagonoma

Glucagon for Injection is contraindicated in patients with insulinoma or glucagonoma as it may cause secondary hypoglycemia. Test patients suspected of having glucagonoma for blood levels of glucagon prior to treatment, and monitor for changes in blood glucose levels during treatment. If a patient develops symptoms of hypoglycemia after a dose of Glucagon for Injection, administer glucose orally or intravenously.

5.3 Hyperglycemia in Patients with Diabetes Mellitus

Treatment with Glucagon for Injection in patients with diabetes mellitus may cause hyperglycemia. Monitor diabetic patients for changes in blood glucose levels during treatment. If patients develop symptoms of hyperglycemia after a dose of Glucagon for Injection, administer insulin.

5.4 Blood Pressure and Heart Rate Increase in Patients with Cardiac Disease

Glucagon for Injection may increase myocardial oxygen demand, blood pressure, and pulse rate which may be life-threatening in patients with cardiac disease. Cardiac monitoring is recommended in patients with cardiac disease during glucagon treatment, and an increase in blood pressure and pulse rate may require therapy.

5.5 Hypersensitivity and Allergic Reactions

Generalized allergic reactions and hypersensitivity, including generalized rash, and anaphylactic shock with breathing difficulties, and hypotension, have been reported with glucagon treatment or lactose. Discontinue Glucagon for Injection and administer standard treatment for anaphylaxis if needed.

6 ADVERSE REACTIONS

The following serious adverse reactions are described below and elsewhere in the labeling:

- Hypertension in patients with Pheochromocytoma [see Contraindications (4) and Warnings and Precautions (5.1)]
- Hypoglycemia in Patients with Insulinoma and Glucagonoma [see Contraindications (4) and Warnings and Precautions (5.2)]
- Hyperglycemia in Patients with Diabetes Mellitus [see Warnings and Precautions (5.3)]
- Hypersensitivity and Allergic Reactions; generalized allergic reactions including generalized rash, and in some cases anaphylactic shock with breathing difficulties, and hypotension [see Warnings and Precautions (5.5)]

Adverse Reactions from Clinical Trials

Because clinical trials are conducted under widely varying conditions, adverse reaction rates observed in the clinical trials of a drug cannot be directly compared to the rates in clinical trials of another drug and may not reflect the rates observed in practice.

In an open-label clinical study of Glucagon for Injection, 29 healthy volunteers received a single dose of 1 mg Glucagon for Injection intramuscularly. Table 1 shows the most common adverse reactions that were not present at baseline and occurred in at least 5% of patients.

Table 1: Adverse Reactions in Healthy Volunteers Who Received Glucagon for Injection, 1 mg Administered Intramuscularly

 | (N=29) % of Patients
Vomiting | 17
Nausea | 7

Adverse Reactions from the Literature and Other Clinical Studies

The following adverse reactions have been identified from the literature and clinical studies with the use of glucagon. Therefore, it is not possible to reliably estimate their frequency.

- Nausea and vomiting occurred with doses above 1 mg administered by rapid intravenous injection (within 1 to 2 seconds). Doses above 1 mg are not recommended for intravenous use [see Dosage and Administration (2.1)].
- Hypotension was reported up to 2 hours after administration in patients receiving glucagon as premedication for upper GI endoscopy procedures.
- A temporary increase in both blood pressure and pulse rate occurred following the administration of glucagon. Patients taking beta-blockers experienced a temporary increase in both pulse and blood pressure that was greater than normal [see Drug Interactions (7)].
- Other adverse reactions included hypoglycemia and hypoglycemic coma, as described in postmarketing reports. Patients taking indomethacin may be more likely to experience hypoglycemia following glucagon administration [see Drug Interactions (7)].

7 DRUG INTERACTIONS

Table 2 includes clinically significant drug interactions with Glucagon for Injection.

Table 2: Clinically Significant Drug Interactions with Glucagon for Injection

Beta-Blockers
Clinical Impact: | The concomitant use of beta-blockers and Glucagon for Injection may increase the risk of a temporary increase in heart rate and blood pressure.
Intervention: | The increase in blood pressure and heart rate may require therapy in patients with coronary artery disease.
Insulin
Clinical Impact: | Insulin reacts antagonistically towards glucagon.
Intervention: | Monitor blood glucose when Glucagon for Injection is used as a diagnostic aid in diabetes patients.
Indomethacin
Clinical Impact: | The concomitant use of indomethacin and Glucagon for Injection may lead to hypoglycemia.
Intervention: | Monitor blood glucose levels during glucagon treatment of patients taking indomethacin.
Anticholinergic Drugs
Clinical Impact: | The concomitant use of anticholinergic drugs and Glucagon for Injection increase the risk of gastrointestinal adverse reactions due to additive effects on inhibition of gastrointestinal motility.
Intervention: | Concomitant use is not recommended.
Warfarin
Clinical Impact: | Glucagon may increase the anticoagulant effect of warfarin.
Intervention: | Monitor patients for unusual bruising or bleeding, as adjustments in warfarin dosage may be required.

8 USE IN SPECIFIC POPULATIONS

8.1 Pregnancy

Pregnancy Category B.

Reproduction studies were performed in rats and rabbits with another glucagon product at doses of 0.4, 2, and 10 mg per kg. These doses represent exposures of up to 100 and 200 times the human dose based on mg/m^2 for rats and rabbits, respectively, and revealed no evidence of harm to the fetus. There are, however, no adequate and well-controlled studies in pregnant women. Glucagon does not cross the human placental barrier.

8.3 Nursing Mothers

It is not known whether glucagon is excreted in human milk. Because many drugs are excreted in human milk, caution should be exercised when glucagon is administered to a nursing woman. No clinical studies have been performed in nursing mothers, however, glucagon is a peptide and intact glucagon is not absorbed from the GI tract. Therefore, even if the infant ingested glucagon it would be unlikely to have any effect on the infant. Additionally, glucagon has a short plasma half-life thus limiting amounts available to the child.

8.4 Pediatric Use

Safety and effectiveness of Glucagon for Injection have not been established in pediatric patients for use as a diagnostic aid during radiologic examinations to temporarily inhibit movement of the gastrointestinal tract.

10 OVERDOSAGE

If overdosage occurs, the patient may experience nausea, vomiting, inhibition of GI tract motility, increase in blood pressure and heart rate, and decrease in serum potassium. In case of suspected overdosage, monitor and correct hypokalemia. If the patient develops a severe increase in blood pressure, phentolamine mesylate may be effective in lowering blood pressure for the short time that control would be needed.

11 DESCRIPTION

Glucagon for Injection, for intravenous or intramuscular use, is a gastrointestinal motility inhibitor that is produced by solid phase peptide synthesis. Glucagon is a single-chain polypeptide containing 29 amino acid residues. The chemical structure of the glucagon polypeptide is identical to human glucagon and to glucagon extracted from beef and pork pancreas. The structure of glucagon is:

C153H225N43O49S Molecular Weight = 3483

Glucagon for Injection is a sterile, lyophilized white powder in a 3 mL vial. The reconstituted solution contains 1 mg of glucagon as hydrochloride per mL and lactose monohydrate (107 mg). Glucagon for Injection is supplied at pH 2.5 to 3.5 and is soluble in water.

12 CLINICAL PHARMACOLOGY

12.1 Mechanism of Action

Extra hepatic effects of glucagon include relaxation of the smooth muscle of the stomach, small bowel, and colon.

12.2 Pharmacodynamics

Table 3 displays the pharmacodynamics properties of Glucagon for Injection as a diagnostic aid during radiologic examination.

Table 3: Pharmacodynamic Properties of Glucagon for Injection as a Diagnostic Aid

Route of Administration | Dosea | Time of Onset of Action for GI Smooth Muscle Relaxation | Duration of Smooth Muscle Relaxation
Intravenous | 0.25 to 0.5 mg | 45 seconds | 9 to 17 minutes
Intramuscular | 1 mg | 8 to 10 minutes | 12 to 27 minutes
Intramuscular | 2 mg | 4 to 7 minutes | 21 to 32 minutes

a Select from these doses based on type of diagnostic procedure, route of administration and procedure duration.

12.3 Pharmacokinetics

Absorption

Following intramuscular administration of 1 mg dose, the maximum plasma glucagon concentrations of 3391 pg/mL were attained approximately 10 minutes after dosing.

Metabolism

The mean apparent half-life of glucagon was 26 minutes after intramuscular administration.

Glucagon is degraded in the liver, kidney, and plasma.

13 NONCLINICAL TOXICOLOGY

13.1 Carcinogenesis, Mutagenesis, Impairment of Fertility

Carcinogenesis

Long term studies in animals to evaluate carcinogenic potential have not been performed.

Mutagenesis

Synthetic glucagon was negative in the bacterial reverse mutation assay (Ames test). The clastogenic potential of synthetic glucagon in the Chinese Hamster Ovary (CHO) assay was positive in the absence of metabolic activation. Doses of 100 and 200 mg/kg of glucagon of both pancreatic and recombinant origins gave slightly higher incidences of micronucleus formation in male mice but there was no effect in females. The weight of evidence indicates that synthetic and recombinant glucagon are not different and do not pose a genotoxic risk to humans.

Impairment of Fertility

Glucagon was not tested in animal fertility studies. Studies in rats have shown that pancreatic glucagon does not cause impaired fertility.

16 HOW SUPPLIED/STORAGE AND HANDLING

16.1 How Supplied

Glucagon for Injection is supplied as a sterile, lyophilized white powder in a vial.

Presentation/ Product Code | Unit of Sale NDC | Strength | Description/Unit of Use NDC
10 Single dose vials NP509613 | 63323-596-16 | 1 mg per vial | 1 mL single dose vial of Glucagon for Injection (NDC 63323-596-08)
Diagnostic Kit NP509603 | 63323-594-03 | 1 mg per vial | 1 mL single dose vial of Glucagon for Injection (NDC 63323-596-06) with 1 mL single dose vial of Sterile Water for Injection, USP for reconstitution (NDC 63323-185-03)

The container closure is not made with natural rubber latex.

16.2 Recommended Storage

Before Reconstitution

The package containing Glucagon for Injection vials may be stored up to 24 months at 20° to 25° C (68° to 77° F) [see USP Controlled Room Temperature] prior to reconstitution. Do not freeze. Keep in the original package to protect from light.

After Reconstitution

The Glucagon for Injection must be reconstituted with Sterile Water for Injection prior to use. Use reconstituted glucagon solution immediately. Discard any unused portion [see Dosage and Administration (2.3)].

17 PATIENT COUNSELING INFORMATION

- Inform patients that generalized allergic reactions have been reported with glucagon treatment including generalized rash, and in some cases anaphylactic shock with breathing difficulties, and hypotension. Advise patients to monitor and report any signs or symptoms of a hypersensitivity reaction [see Warnings and Precautions (5.5)].
- Inform patients that hypoglycemia has occurred with treatment with glucagon. Inform patients of the symptoms of hypoglycemia and how to treat it. Advise patients to avoid driving or operating machinery until ingesting a meal. Advise patients to inform their health care provider if hypoglycemia occurs so that treatment may be given if necessary [see Adverse Reactions (6)].
- Inform patients with diabetes mellitus that treatment with Glucagon for Injection may increase their risk of hyperglycemia [see Warnings and Precautions (5.3)].
- Inform patients with cardiac disease that treatment with Glucagon for Injection may increase their risk of a transient increase in blood pressure and heart rate [see Warnings and Precautions (5.4)].

Novaplus is a registered trademark of Vizient, Inc.
Manufactured by:
Fresenius Kabi
Lake Zurich, IL 60047
www.fresenius-kabi.com/us

451462B

PACKAGE LABEL

PACKAGE LABEL - PRINCIPAL DISPLAY - Glucagon Kit 1 mg Vial Label
NP509603
Glucagon
for Injection
(Synthetic)
1 mg per vial
For intramuscular or
intravenous injection.
For diagnostic use only.
Reconstitute with Sterile Water
for Injection, USP Rx only

PACKAGE LABEL

PACKAGE LABEL - PRINCIPAL DISPLAY - Glucagon Kit Sterile Water 1 mL Vial Label
Sterile Water
for Injection, USP
1 mL per vial
FOR DRUG DILUENT USE ONLY

Contains no antimicrobial or
other added substance. Do not
give intravenously unless
rendered nearly Isotonic.
Discard unused portion.
1 mL Single Dose Vial Rx only

PACKAGE LABEL

PACKAGE LABEL - PRINCIPAL DISPLAY - Glucagon Kit 1 mg Vial Carton Panel
63323-594-03 NP509603
Glucagon
for Injection
(Synthetic)
For intramuscular or
intravenous injection only.
1 mg per vial
FOR DIAGNOSTIC USE ONLY.
Reconstitute with Sterile Water
for Injection, USP immediately before use.
Each kit contains:

- One single dose vial with 1 mg of Glucagon for Injection
- One single dose vial with 1 mL of Sterile Water for Injection, USP

Single Dose Vials
Rx only

PACKAGE LABEL

PACKAGE LABEL - PRINCIPAL DISPLAY - Glucagon 1 mg Vial Label
NP509613
Glucagon
for Injection
(Synthetic)
1 mg per vial
For intramuscular
or intravenous injection.
For diagnostic use only.
Reconstitute with Sterile Water
for Injection, USP Rx only

PACKAGE LABEL

PACKAGE LABEL - PRINCIPAL DISPLAY - Glucagon 1 mg Vial Tray Label
NDC 63323-596-16
Glucagon
for Injection
(Synthetic)
For intramuscular or intravenous injection only.
1 mg per vial
For diagnostic use only.
10 Single Dose Vials Rx only